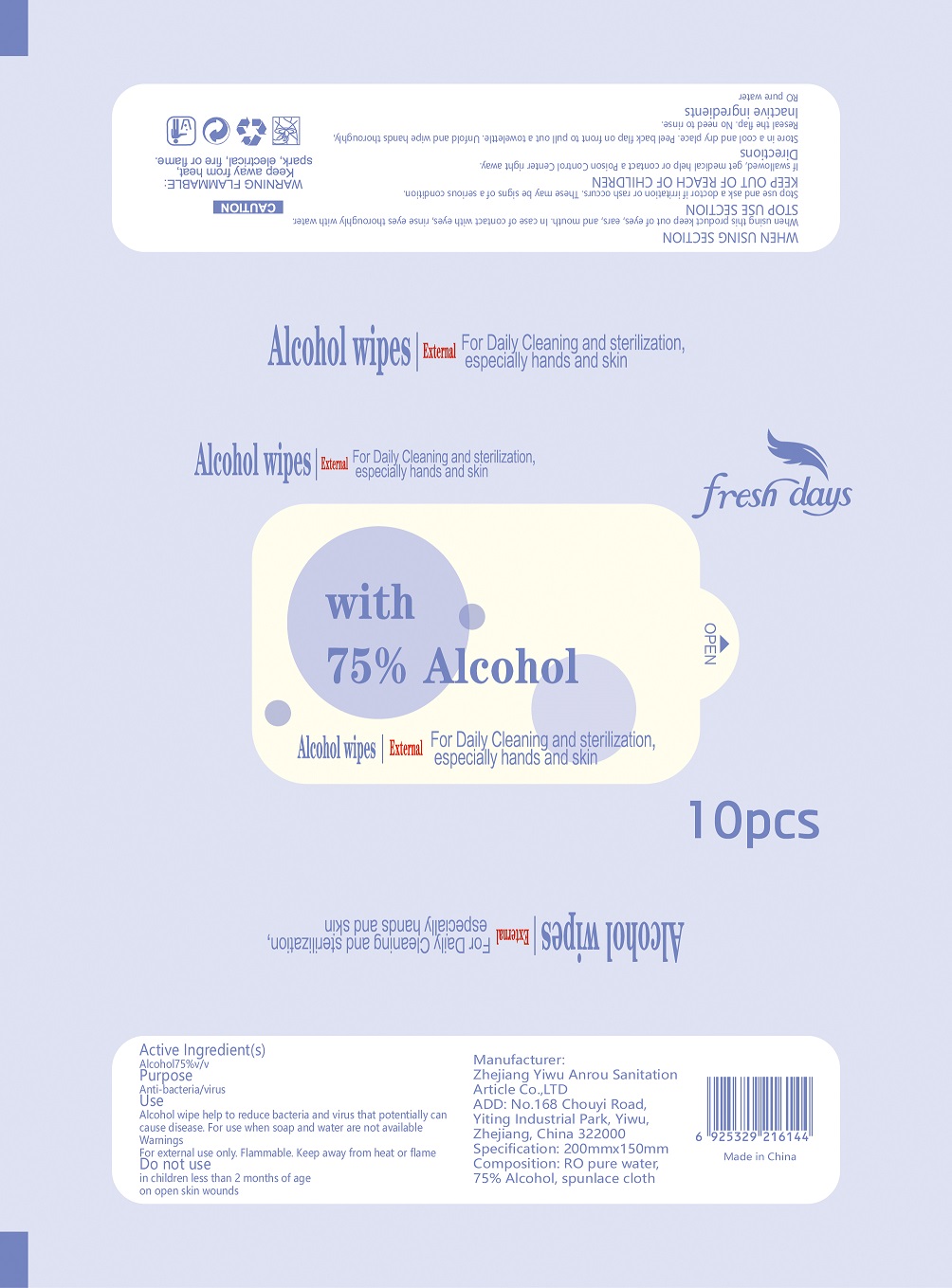 DRUG LABEL: Alcohol Wipes
NDC: 78356-102 | Form: CLOTH
Manufacturer: Zhejiang Yiwu Anrou Sanitation Article Co., Ltd
Category: otc | Type: HUMAN OTC DRUG LABEL
Date: 20200609

ACTIVE INGREDIENTS: ALCOHOL 3.125 mL/1 1
INACTIVE INGREDIENTS: WATER

Anrou, Sanitizing Wipes, 75% Alcohol, *10 wipes

Active ingredient

Alcohol 75% v/v. Purpose: Anti-bacteria/virus

Purpose

Anti-bacteria/virus.

When Using

When using this product keep out of eyes, ears, and mouth.

In case of contact with eyes, rinse eyes throughly with water.

Do not use

- in children less than 2 months of age
- on open skin wounds

Stop use

Stop use and ask a doctor if irritation or rash occurs. These may be signs of a serious condition.

KEEP OUT OF REACH OF CHILDREN

If swallowed, get medical help or contact a Poison Control Center right away.

Indications & usage

Alcohol wipe help to reduce bacteria and virus that potentially can cause disease. For use when soap and water are not available.

Directions

Peel back flap on front to pull out a towelettle.

Unfold and wipes hands thoroughly.

Reseal the flap.

No need to rinse.

Warnings

For external use only.

Flammable, keep away from heat, spark, electrical, fire or flame.

Other information

Store at room temperature.

Inactive ingredient

RO pure water.